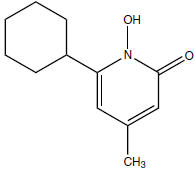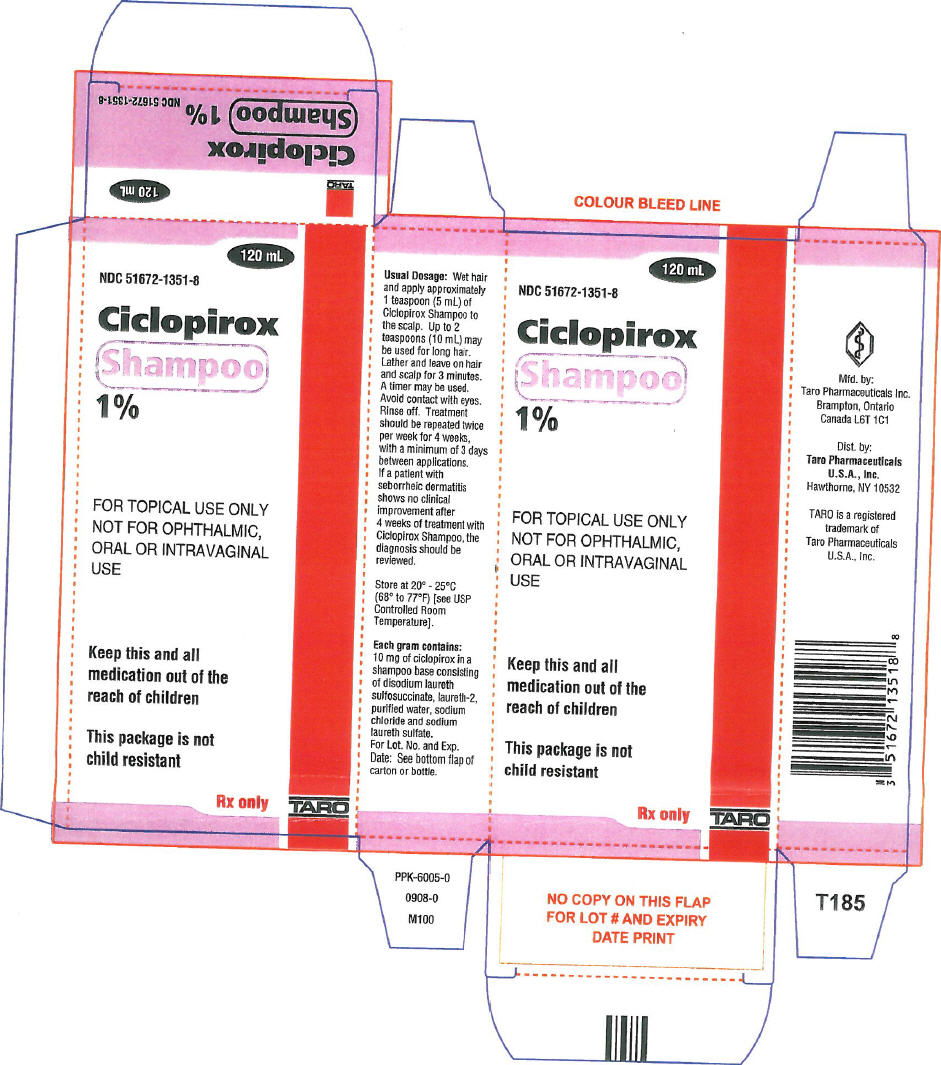 DRUG LABEL: Ciclopirox
NDC: 61360-1351 | Form: SHAMPOO
Manufacturer: Taro Pharmaceuticals, Inc.
Category: prescription | Type: HUMAN PRESCRIPTION DRUG LABEL
Date: 20111118

ACTIVE INGREDIENTS: ciclopirox 10 mg/0.96 mL
INACTIVE INGREDIENTS: disodium laureth sulfosuccinate; laureth-2; water; sodium chloride; sodium laureth sulfate

Ciclopirox Shampoo, 1%

Rx Only

FOR TOPICAL USE ONLY
NOT FOR OPHTHALMIC, ORAL OR INTRAVAGINAL USE
KEEP OUT OF REACH OF CHILDREN

DESCRIPTION

Ciclopirox Shampoo 1% contains the synthetic antifungal agent, ciclopirox.

Each gram (equivalent to 0.96 mL) of Ciclopirox Shampoo contains 10 mg ciclopirox in a shampoo base consisting of disodium laureth sulfosuccinate, laureth-2, purified water USP, sodium chloride USP and sodium laureth sulfate.

Ciclopirox Shampoo is a colorless to yellowish, translucent solution. The chemical name for ciclopirox is 6-cyclohexyl-1-hydroxy-4-methyl-2(1H)-pyridone, with the empirical formula C12H17NO2 and a molecular weight of 207.27. The CAS Registry Number is [29342-05-0]. The chemical structure is:

CLINICAL PHARMACOLOGY

Mechanism of Action

Ciclopirox is a hydroxypyridone antifungal agent although the relevance of this property for the indication of seborrheic dermatitis is not known. Ciclopirox acts by chelation of polyvalent cations (Fe^3+ or Al^3+), resulting in the inhibition of the metal-dependent enzymes that are responsible for the degradation of peroxides within the fungal cell.

Pharmacokinetics and Pharmacodynamics

In a study in patients with seborrheic dermatitis of the scalp, application of 5 mL ciclopirox shampoo 1% twice weekly for 4 weeks, with an exposure time of 3 minutes per application, resulted in detectable serum concentrations of ciclopirox in 6 out of 18 patients. The serum concentrations measured throughout the dosing interval on Days 1 and 29 ranged from 10.3 ng/mL to 13.2 ng/mL. Total urinary excretion of ciclopirox was less than 0.5% of the administered dose.

CLINICAL STUDIES

In two randomized, double-blind clinical trials, patients 16 years and older with seborrheic dermatitis of the scalp applied Ciclopirox Shampoo or its vehicle two times per week for 4 weeks. Patients who were immunocompromised, those with psoriasis or atopic dermatitis, women of childbearing potential not using adequate contraception, and pregnant or lactating women were excluded from the clinical studies. An evaluation of the overall status of the seborrheic dermatitis, and the presence and severity of erythema or inflammation, and scaling, was made at week 4, using a scale of 0 = none, 1 = slight, 2 = mild, 3 = moderate, 4 = pronounced, and 5 = severe. Effective treatment was defined as achieving a score of 0 (or a score of 1 if the baseline score was ≥ 3) simultaneously for status of the seborrheic dermatitis, erythema or inflammation, and scaling at Week 4. Ciclopirox shampoo was shown to be statistically significantly more effective than vehicle in both studies. Efficacy results for the two studies are presented in the following table.

Effective Treatment Rates at Week 4 in Studies 1 and 2
 | Ciclopirox Shampoo | Vehicle
Study 1 | 220/380 (58%) | 60/192 (31%)
Study 2 | 65/250 (26%) | 32/249 (13%)

Efficacy for black patients was not demonstrated, although only 53 black patients were enrolled in the two pivotal studies.

Microbiology

Ciclopirox is fungicidal in vitro against Malassezia furfur (Pityrosporum spp.), P. ovale, and P. orbiculare. Ciclopirox acts by chelation of polyvalent cations (Fe^3+ or Al^3+), resulting in the inhibition of the metal-dependent enzymes that are responsible for the degradation of peroxides within the fungal cell.

The clinical significance of antifungal activity in the treatment of seborrheic dermatitis is not known.

INDICATIONS AND USAGE

Ciclopirox Shampoo is indicated for the topical treatment of seborrheic dermatitis of the scalp in adults.

CONTRAINDICATIONS

Ciclopirox Shampoo is contraindicated in individuals who have shown hypersensitivity to any of its components.

WARNINGS

Ciclopirox Shampoo is not for ophthalmic, oral, or intravaginal use.

Keep out of reach of children.

PRECAUTIONS

General

If a reaction suggesting sensitivity or irritation should occur with the use of Ciclopirox Shampoo, treatment should be discontinued and appropriate therapy instituted.

Contact of Ciclopirox Shampoo with the eyes should be avoided. If contact occurs, rinse thoroughly with water.

Seborrheic dermatitis may appear at puberty, however, no clinical studies have been done in patients younger than 16 years.

In patients with lighter hair color, hair discoloration has been rarely reported.

There is no relevant clinical experience with patients who have a history of immunosuppression (e.g., extensive, persistent, or unusual distribution of dermatomycoses, recent or recurring herpes zoster, or persistent herpes simplex), who are immunocompromised (e.g., HIV-infected patients and transplant patients), or who have a diabetic neuropathy.

Information for Patients

The patient should be instructed to:

1. Use Ciclopirox Shampoo as directed by the physician. Avoid contact with the eyes and mucous membranes. If contact occurs, rinse thoroughly with water. Ciclopirox Shampoo is for external use on the scalp only. Do not swallow.
2. Use the medication for seborrheic dermatitis for the full treatment time even though symptoms may have improved. Notify the physician if there is no improvement after 4 weeks.
3. Inform the physician if the area of application shows signs of increased irritation (redness, itching, burning, blistering, swelling, or oozing) indicative of possible allergic reaction.
4. Not use the medication for any disorder other than that for which it is prescribed.

Carcinogenesis, Mutagenesis, and Impairment of Fertility

Long-term animal studies have not been performed to evaluate the carcinogenic potential of Ciclopirox Shampoo or ciclopirox.

The following in vitro genotoxicity tests have been conducted with ciclopirox: evaluation of gene mutation in the Ames Salmonella and E. coli assays (negative); chromosome aberration assays in V79 Chinese hamster lung fibroblast cells, with and without metabolic activation (positive); chromosome aberration assays in V79 Chinese hamster lung fibroblast cells in the presence of supplemental Fe^3+, with and without metabolic activation (negative); gene mutation assays in the HGPRT-test with V79 Chinese hamster lung fibroblast cells (negative); and a primary DNA damage assay (i.e., unscheduled DNA synthesis assay in A549 human cells) (negative). An in vitro cell transformation assay in BALB/c 3T3 cells was negative for cell transformation. In an in vivo Chinese hamster bone marrow cytogenetic assay, ciclopirox was negative for chromosome aberrations at a dosage of 5000 mg/kg body weight.

A combined oral fertility and embryofetal developmental study was conducted in rats with ciclopirox olamine. No effect on fertility or reproductive performance was noted at the highest dose tested of 3.85 mg/kg/day ciclopirox (approximately 1.3 times the maximum recommended human dose based on body surface area comparisons).

Pregnancy

Teratogenic effects

Pregnancy Category B

Oral embryofetal developmental studies were conducted in mice, rats, rabbits and monkeys. Ciclopirox or ciclopirox olamine was orally administered during the period of organogenesis. No maternal toxicity, embryotoxicity or teratogenicity were noted at the highest doses of 77, 125, 80 and 38.5 mg/kg/day ciclopirox in mice, rats, rabbits and monkeys, respectively (approximately 13, 42, 54 and 26 times the maximum recommended human dose based on body surface area comparisons, respectively).

Dermal embryofetal developmental studies were conducted in rats and rabbits with ciclopirox olamine dissolved in PEG 400. Ciclopirox olamine was topically administered during the period of organogenesis. No maternal toxicity, embryotoxicity or teratogenicity were noted at the highest doses of 92 mg/kg/day and 77 mg/kg/day ciclopirox in rats and rabbits, respectively (approximately 31 and 54 times the maximum recommended human dose based on body surface area comparisons, respectively).

There are no adequate or well-controlled studies of topically applied ciclopirox in pregnant women. Because animal reproduction studies are not always predictive of human response, Ciclopirox Shampoo should be used during pregnancy only if clearly needed.

Nursing Mothers

It is not known whether this drug is excreted in human milk. Because many drugs are excreted in human milk, caution should be exercised when Ciclopirox Shampoo is administered to a nursing woman.

Pediatric Use

Seborrheic dermatitis may appear at puberty, however, no clinical studies have been done in patients younger than 16 years.

Geriatric Use

In clinical studies, the safety and tolerability of Ciclopirox Shampoo in the population 65 years and older was comparable to that of younger subjects. Results of the efficacy analysis in those patients 65 years and older showed effectiveness in 25 of 85 (29%) patients treated with Ciclopirox Shampoo, and in 15 of 61 (25%) patients treated with the vehicle; due to the small sample size, a statistically significant difference was not demonstrated. Other reported clinical experience has not identified differences in responses between the elderly and younger subjects, but greater sensitivity to adverse effects in some older individuals cannot be ruled out.

ADVERSE REACTIONS

In 626 patients treated with Ciclopirox Shampoo twice weekly in the two pivotal clinical studies, the most frequent adverse events were increased itching in 1% of patients, and application site reactions, such as burning, erythema, and itching, also in 1% of patients. Other adverse events occurred in individual patients only.

Adverse events that led to early study medication termination in clinical trials occurred in 1.5% (26/1738) of patients treated with Ciclopirox Shampoo and 2.0% (12/661) of patients treated with shampoo vehicle. The most common adverse events leading to termination of study medication in either group was seborrhea. In the Ciclopirox Shampoo group, other adverse events included rash, pruritus, headache, ventricular tachycardia, and skin disorder. In the shampoo vehicle group, other adverse events included skin disorder and rash.

DOSAGE AND ADMINISTRATION

Wet hair and apply approximately 1 teaspoon (5 mL) of Ciclopirox Shampoo to the scalp. Up to 2 teaspoons (10 mL) may be used for long hair. Lather and leave on hair and scalp for 3 minutes. A timer may be used. Avoid contact with eyes. Rinse off. Treatment should be repeated twice per week for 4 weeks, with a minimum of 3 days between applications.

If a patient with seborrheic dermatitis shows no clinical improvement after 4 weeks of treatment with Ciclopirox Shampoo, the diagnosis should be reviewed.

HOW SUPPLIED

STORAGE AND HANDLING

Ciclopirox Shampoo, 1% is supplied in 120 mL plastic bottles (NDC 51672-1351-8). Discard unused product after initial treatment duration. Store at 20° - 25°C (68° - 77°F) [See USP Controlled Room Temperature].

Mfd. By: Taro Pharmaceuticals Inc., Brampton, Ontario, Canada L6T 1C1

Dist. By: Taro Pharmaceuticals U.S.A., Inc., Hawthorne, NY 10532

Issued: September, 2008

PPK-6006-0
266

PRINCIPAL DISPLAY PANEL - 120 mL Carton

120 mL

NDC 51672-1351-8

Ciclopirox
Shampoo
1%

FOR TOPICAL USE ONLY
NOT FOR OPHTHALMIC,
ORAL OR INTRAVAGINAL
USE

Keep this and all
medication out of the
reach of children

This package is not
child resistant

Rx only

TARO